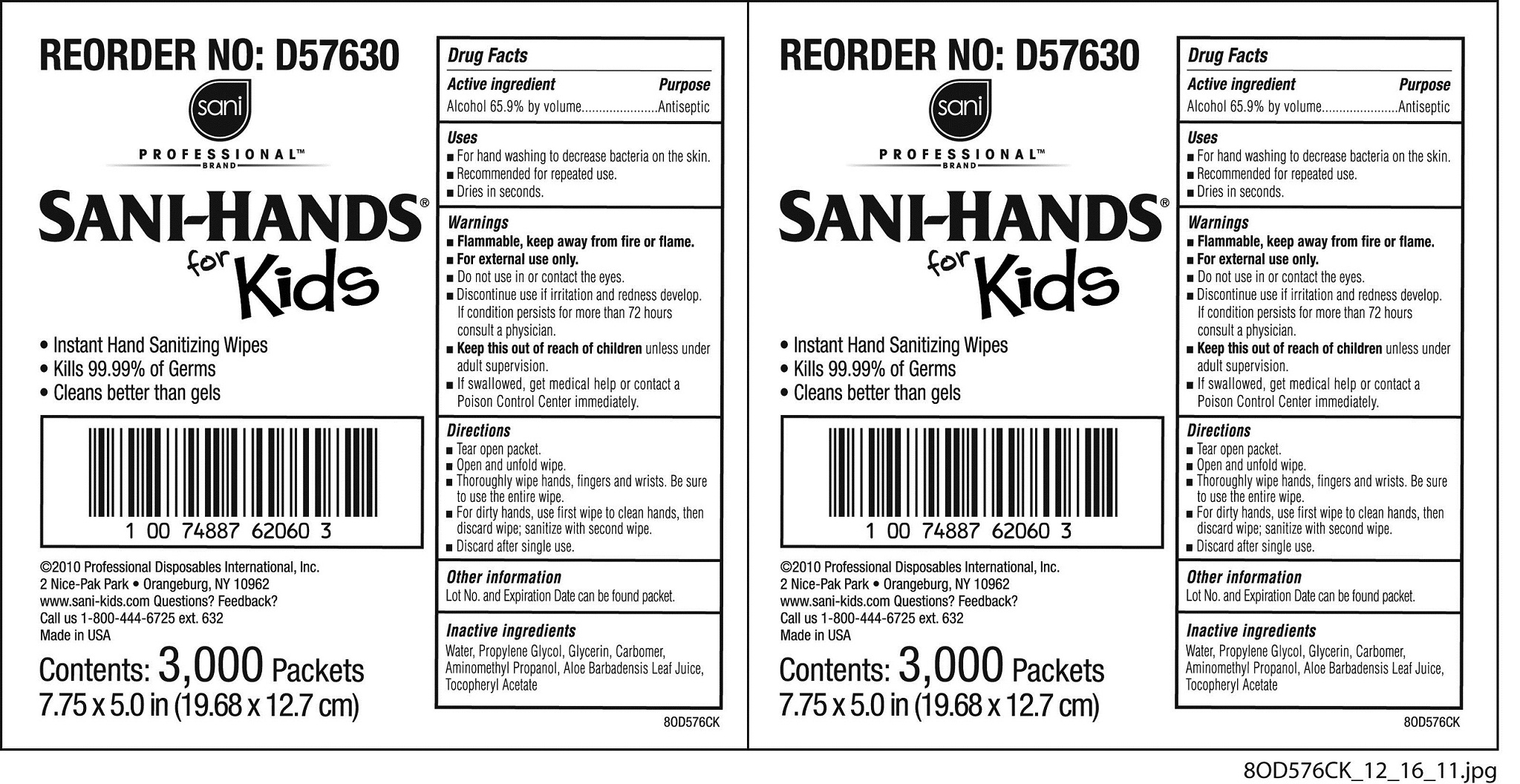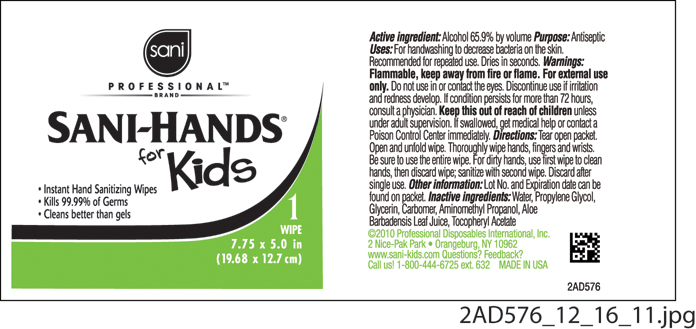 DRUG LABEL: Sani-Hands
NDC: 10819-6003 | Form: CLOTH
Manufacturer: Professional Disposables International, Inc.
Category: otc | Type: HUMAN OTC DRUG LABEL
Date: 20120109

ACTIVE INGREDIENTS: Alcohol 0.659 mL/1 1
INACTIVE INGREDIENTS: WATER; PROPYLENE GLYCOL; GLYCERIN; CARBOMER HOMOPOLYMER TYPE C; AMINOMETHYL PROPANEDIOL; ALOE VERA LEAF; ALPHA-TOCOPHEROL ACETATE

SANI PROFESSIONAL BRAND SANI-HANDS FOR KIDS INSTANT HAND SANITIZING WIPES

Uses

- For hand washing to decrease bacteria on the skin.
- Recommended for repeated use.
- Dries in seconds.

Warnings

- Flammable, keep away from fire or flame.
- For external use only.
- Do not use in or contact the eyes.
- Discontinue use if irritation and redness develop. If condition persist for more than 72 hours consult a physician.
- If swallowed, get medical help or contact a Poison Control Center right away.

KEEP OUT OF REACH OF CHILDREN

- Keep this out of reach of children unless under adult supervision.

Directions

- Tear open packet
- Open and unfold wipe.
- Thoroughly wipe hands, fingers and wrists. Be sure to use the entire wipe.
- For dirty hands, use first wipe to clean hands, then discard wipe; sanitize with second wipe.
- Discard after single use.

Other information

Lot No. and Expiration Date can be found on packet.

Dosage

For dirty hand, use first wipe to clean hands, then discard wipe; sanitize with second wipe. Discard after single use.

Inactive ingredients

Water, Propylene Glycol, Glycerin, Carbomer, Aminometyl Propanol, Aloe Barbadensis Leaf Juice, Tocopheryl Acetate

Professional Disposables International, Inc.
2 Nice-Pak Park
Orangeburg, NY 10962-1376
www.sani-kids.com Questions? Feedback?
Call us 1-800-444-6725 ext. 632
Made in USA

Principal Display Panel - 3000 Packets per Case

Sani
Professional Brand
SANI-HANDS(R)
for Kids

- Instant Hand Sanitizing Wipes
- Kills 99.99% of Germs
- Cleans better than gels

Contents: 3000 Packets per Case
7.75 x 5.0 in (19.68 x 12.7 cm)
Packet Label
Case Label

Active ingredient

Alcohol 65.9% by volume

Purpose

Antiseptic